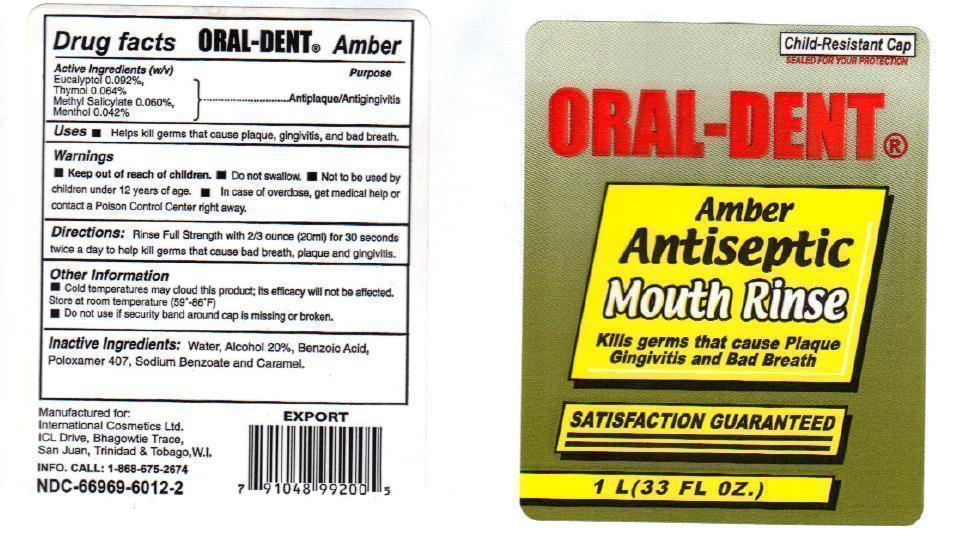 DRUG LABEL: Oral Dent
NDC: 66969-6012 | Form: MOUTHWASH
Manufacturer: International Cosmetic Limited
Category: otc | Type: HUMAN OTC DRUG LABEL
Date: 20140315

ACTIVE INGREDIENTS: EUCALYPTOL 0.092 g/100 mL; THYMOL 0.064 g/100 mL; METHYL SALICYLATE 0.060 g/100 mL; MENTHOL 0.042 g/100 mL
INACTIVE INGREDIENTS: WATER; ALCOHOL; BENZOIC ACID; POLOXAMER 407; SODIUM BENZOATE; CARAMEL

Oral Dent Amber

Active ingredients (W/V)

Eucalyptol 0.092%
Thymol 0.064%
Methyl Salicylate 0.060%
Menthol 0.042%

Purpose

Antiplaque/Antigingivitis

Keep out of reach of children.

In case of overdose, get medical help or contact a Poison Control Center right away.

Uses

Helps kill germs that cause plaque, gingivitis and bad breath.

Warnings

- Do not swallow
- Not to be used by children under 12 years of age

Directions

Rinse Full Strength with 2/3 ounce (20 ml) for 30 seconds twice a day to help kill germs that cause bad breath, plaque and gingivitis.

Other information

- Cold temperature may cloud this product; its efficacy will not be affected. Store at room temperature (59^0-86^0 F)

- Do not use if security band around cap is missing or broken.

Inactive ingredients

Water, Alcohol 20%, Benzoic Acid, Poloxamer 407, Sodium Benzoate and Caramel.

Manufactured for

International Cosmetics Ltd.

ICL Drive, Bhagowtie Trace,

San Juan, Trinidad & Tobago, W.I.

INFO. CALL:1-868-675-2674